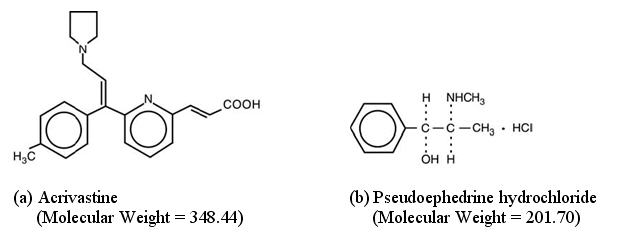 DRUG LABEL: Unknown
Manufacturer: UCB, Inc.
Category: prescription | Type: HUMAN PRESCRIPTION DRUG LABEL
Date: 20080527

Semprex®-D Capsules
(acrivastine and pseudoephedrine hydrochloride)

DESCRIPTION

SEMPREX-D Capsules (acrivastine and pseudoephedrine hydrochloride) are a fixed combination product formulated for oral administration. Acrivastine is an antihistamine and pseudoephedrine is a decongestant. Each capsule contains 8 mg acrivastine and 60 mg pseudoephedrine hydrochloride and the inactive ingredients: lactose, magnesium stearate and sodium starch glycolate. The green and white capsule shell consists of gelatin, D&C Yellow No. 10, FD&C Green No. 3, and titanium dioxide. The yellow band around the capsule consists of gelatin and D&C Yellow No. 10. The capsules may contain one or more parabens and are printed with edible black and white inks.

The chemical name of acrivastine is (E,E)-3-[6-[1-(4-methylphenyl)-3-(1-pyrrolidinyl)-1-propenyl]-2-pyridinyl]-2-propenoic acid; the molecular formula is C22H24N2O2. As an analog of triprolidine hydrochloride, acrivastine is classified as an alkylamine antihistamine. Acrivastine is an odorless, white to pale cream crystalline powder that is soluble in chloroform and alcohol and slightly soluble in water.

The chemical name of pseudoephedrine hydrochloride is [S-(R*,R*)]-α-[1-(methylamino)ethyl]benzenemethanol hydrochloride; the molecular formula is C10H15NO•HCl. Pseudoephedrine is one of the naturally occurring dextrorotatory diastereoisomers of ephedrine and is classified as an indirect sympathomimetic amine. Pseudoephedrine hydrochloride occurs as odorless, fine white to off-white crystals or powder; the drug is soluble in water, alcohol and chloroform.

Structural formulae for the active ingredients of SEMPREX-D Capsules are as follows:

CLINICAL PHARMACOLOGY

Acrivastine, a structural analog of triprolidine hydrochloride, exhibits H1-antihistaminic activity in isolated tissues, animals, and humans, and has sedative effects in humans (see PRECAUTIONS). The propionic acid derivative of acrivastine is a metabolite in several animal species (as well as in man) and also exhibits H1-antihistaminic activity.

Pseudoephedrine hydrochloride is an indirect sympathomimetic agent; that is, it releases norepinephrine from adrenergic nerves.

In vitro test and in vivo studies in animals of acrivastine and pseudoephedrine in combination failed to demonstrate evidence of any beneficial or deleterious pharmacologic interaction between the two agents.

Pharmacokinetics And Metabolism

Acrivastine was absorbed rapidly from the combination capsule following oral administration and was as bioavailable as a solution of acrivastine. After administration of SEMPREX-D Capsules, maximum plasma acrivastine concentrations were achieved at 1.14 ± 0.23 hour. A mass balance study in 7 healthy volunteers showed that acrivastine is primarily eliminated by the kidneys. Over a 72-hour collection period, about 84% of the administered total radioactivity was recovered in urine and about 13% in feces, for a combined recovery of about 97%. Further, 67% of the administered radioactive dose was recovered in urine as the unchanged drug, 11% as the propionic acid metabolite, and 6% as other unknown metabolites.

Acrivastine exhibits linear kinetics over dosages ranging from 2 to 32 mg t.i.d. The mean ± SD terminal half-life for acrivastine was 1.9 ± 0.3 hours following single oral doses and increased to 3.5 ± 1.9 hours at steady state. The terminal half-life for the propionic acid metabolite was 3.8 ± 1.4 hours. Because of the short half-lives of both acrivastine and its metabolites, accumulation in the plasma following multiple dosing is not expected.

The steady-state maximum acrivastine plasma concentration was 227 ± 47 ng/mL. The oral clearance, and apparent volume of distribution were 2.9 ± 0.7 mL/min/kg and 0.46 ± 0.05 L/kg, respectively, following a single oral dose; oral clearance did not change at steady state (2.86 ± 0.75 mL/min/kg). The apparent volume of distribution increased to 0.82 ± 0.6 L/kg to parallel the increase in the elimination half-life of the drug.

Acrivastine binding to human plasma proteins was 50 ± 2.0% and was concentration-independent over the range of 5 to 1000 ng/mL. The main binding protein was serum albumin although the drug was slightly bound to α-1-acid glycoprotein. No displacement interaction was observed between acrivastine and either phenytoin or theophylline. The binding of acrivastine was not affected by the presence of pseudoephedrine.

Pseudoephedrine hydrochloride was also rapidly absorbed from the combination capsule, and the capsule was as bioavailable as a solution of pseudoephedrine. Steady state maximum plasma concentration for pseudoephedrine was 498 ± 129 ng/mL. The terminal half-life, oral clearance and apparent volume of distribution were 6.2 ± 1.8 hours, 5.9 ± 1.7 mL/min/kg, and 3.0 ± 0.4 L/kg, respectively. Elimination of pseudoephedrine is primarily through the renal route as 55 to 75% of an administered dose appears unchanged in the urine. Pseudoephedrine elimination, however, is highly dependent upon urine pH; the plasma half-life decreased to about 4 hours at pH 5 and increased to 13 hours at pH 8.

Pseudoephedrine did not bind to human plasma proteins over the concentration range of 50 to 2000 ng/mL.

Acrivastine and pseudoephedrine do not influence the pharmacokinetics of the other drug when administered concomitantly.

Special Populations

A single dose pharmacokinetic study showed that the elimination half-lives of acrivastine, the propionic acid metabolite of acrivastine, and pseudoephedrine were prolonged in patients with chronic renal insufficiency. Compared to normal volunteers, the elimination half-life of acrivastine was about 50% increased in patients with mild renal insufficiency (creatinine clearance = 26 to 48 mL/min) and was increased by about 130% in patients with moderate (creatinine clearance = 12 to 17 mL/min) or severe (creatinine clearance 6 to 10 mL/min) renal insufficiency. Oral clearance of acrivastine was diminished by the same magnitude as the half-life was prolonged in each of the three renally impaired groups. The elimination half-life of the propionic acid metabolite of acrivastine was about 140% increased in patients with mild renal insufficiency and about 5 times increased in patients with moderate or severe renal insufficiency.

Compared to normal volunteers, the elimination half-life of pseudoephedrine was about 3 times increased in patients with mild renal insufficiency, about 7 times increased in patients with moderate renal insufficiency, and about 10 times increased in patients with severe renal insufficiency. Oral clearance of pseudoephedrine was diminished by about the same magnitude as the half-life was prolonged in each of the three renally impaired groups (see PRECAUTIONS, Use In Patients With Diminished Renal Function).

The total body load removed by dialysis is approximately 20%, 27% and 38% for acrivastine, the propionic acid metabolite of acrivastine, and pseudoephedrine, respectively, and therefore, a supplemental dose after a dialysis session is not required.

Based on a multiple dose cross study comparison, the apparent volume of distribution for acrivastine was 44% lower in elderly (n = 36, 65-75 yr) than in young volunteers (n = 16, 19-33 yr). This difference could be attributed to the decrease in total body water that occurs with aging. Despite this difference, no appreciable differences in plasma acrivastine concentrations were seen in the elderly compared to the young, and no appreciable accumulation of acrivastine occurred in plasma at steady-state. The elimination half-life for pseudoephedrine was 18% longer in elderly (7.9 hours) than in younger subjects (6.7 hours), presumably due to the decline in average renal function that occurs with aging. Despite this difference, clearance of pseudoephedrine was not appreciably different in elderly and younger subjects. Elderly patients can therefore be given the same dosage as younger patients. SEMPREX-D Capsules are not recommended, however, in patients with renal impairment (see PRECAUTIONS, Use In Patients With Diminished Renal Function and Geriatric Use).

The effect of age and sex on the pharmacokinetic parameters of acrivastine and pseudoephedrine was determined in 93 healthy volunteers who participated in various studies. All of the 93 volunteers were Caucasian (81 males and 12 females); 57 were between the ages of 18 and 38 years and 36 were between the ages of 65 and 75 years. There were no age- or sex-related differences in the pharmacokinetic parameters of either acrivastine or pseudoephedrine.

The effect of race on acrivastine and pseudoephedrine pharmacokinetics was examined by screening data obtained from 1035 patients, age 12 to 71 years, who participated in the eight safety and efficacy studies. No race-related differences were observed in the pharmacokinetics of either acrivastine or pseudoephedrine.

CLINICAL STUDIES

In healthy volunteers, histamine-induced wheal and flare areas were significantly reduced relative to placebo at 30 minutes after administration of a single dose of acrivastine 8 mg. Maximum reductions of wheal and flare occurred by 1 to 2 hours and significant reductions relative to placebo persisted for up to 6 hours after a single oral dose of acrivastine 8 mg. No additional reductions of wheal and flare were observed following single doses of acrivastine up to 24 mg. The exact correlation between responses on skin testing and clinical efficacy is not established.

Five randomized, placebo- and/or active-controlled trials compared SEMPREX-D with its acrivastine and pseudoephedrine components for the symptomatic relief of seasonal allergic rhinitis. In these studies, 696 patients received four daily doses of acrivastine 8 mg plus pseudoephedrine hydrochloride 60 mg (i.e., SEMPREX-D Capsules or bioequivalent formulations administered concurrently) or the same doses of the components for 14 days. The combination reduced the intensity of sneezing, rhinorrhea, pruritus, and lacrimation more than pseudoephedrine and reduced the intensity of nasal congestion more than acrivastine, demonstrating a contribution of each of the components. The onset of antihistaminic and nasal decongestant actions occurred within one or two hours after the first dose of SEMPREX-D Capsules. Somnolence occurred in about 12% of patients given SEMPREX-D compared with about 6% on placebo.

INDICATIONS AND USAGE

SEMPREX-D Capsules are indicated for relief of symptoms associated with seasonal allergic rhinitis such as sneezing, rhinorrhea, pruritus, lacrimation, and nasal congestion. SEMPREX-D Capsules should be administered when both the antihistaminic activity of acrivastine and the nasal decongestant activity of pseudoephedrine are desired (see CLINICAL PHARMACOLOGY). The efficacy of SEMPREX-D Capsules beyond 14 days of continuous treatment in patients with seasonal allergic rhinitis has not been adequately investigated in clinical trials.

SEMPREX-D Capsules have not been adequately studied for effectiveness in relieving the symptoms of the common cold.

CONTRAINDICATIONS

SEMPREX-D Capsules are contraindicated in patients with a known sensitivity to acrivastine, other alkylamine antihistamines (e.g., triprolidine), pseudoephedrine, other sympathomimetic amines (e.g., phenylpropanolamine), or to any other components of the formulation. SEMPREX-D Capsules are contraindicated in patients with severe hypertension or severe coronary artery disease. SEMPREX-D Capsules are contraindicated in patients taking monoamine oxidase (MAO) inhibitors and for 14 days after stopping use of an MAO inhibitor (see Drug Interactions).

WARNINGS

SEMPREX-D Capsules should be used with caution in patients with hypertension, diabetes mellitus, ischemic heart disease, increased intraocular pressure, hyperthyroidism, prostatic hypertrophy, stenosing peptic ulcer, or pyloroduodenal obstruction. Overdose of sympathomimetic amines may produce CNS stimulation with convulsions or cardiovascular collapse with accompanying hypotension. The elderly are more likely to have adverse reactions to sympathomimetic amines.

PRECAUTIONS

General

Acrivastine is sedating in some patients. In controlled clinical trials, somnolence (i.e., drowsiness, sedation, sleepiness) was more common with SEMPREX-D Capsules (by an average of 6%) than with placebo (see ADVERSE EXPERIENCES).

Patients should be advised to assess their individual responses to SEMPREX-D Capsules before engaging in any activity requiring mental alertness, such as driving a motor vehicle or operating machinery. Concurrent use of SEMPREX-D Capsules with alcohol or other CNS depressants may cause additional reductions in alertness and impairment of CNS performance and should be avoided (see Drug Interactions).

Use In Patients With Diminished Renal Function

Acrivastine and pseudoephedrine are excreted primarily through the kidney. Both compounds therefore accumulate in patients with impaired renal function. Due to the differential effects of renal failure on the serum half-life and clearance of acrivastine and pseudoephedrine, use of SEMPREX-D Capsules, a fixed combination product, in patients with renal impairment (creatinine clearance ≤ 48 mL/min) is not recommended (see OVERDOSAGE and CLINICAL PHARMACOLOGY).

Information To Patients

Patients taking SEMPREX-D Capsules should receive the following information. SEMPREX-D Capsules are prescribed to reduce symptoms associated with seasonal allergic rhinitis. Patients should be instructed to take SEMPREX-D Capsules only as prescribed and not to exceed the prescribed dose. Patients should be advised against the concurrent use of SEMPREX-D with over-the-counter antihistamines and decongestants. Patients who are or may become pregnant should be told that this product should be used in pregnancy or during lactation only if the potential benefit justifies the potential risks to the fetus or nursing infant. Due to the risk of hypertensive crisis, patients should be instructed not to take SEMPREX-D Capsules (acrivastine and pseudoephedrine hydrochloride) if they are presently taking a monoamine oxidase inhibitor or for 14 days after stopping use of an MAO inhibitor. Patients should be advised to assess their individual responses to SEMPREX-D Capsules before engaging in any activity requiring mental alertness, such as driving a car or operating machinery. Patients should be advised that the concurrent use of SEMPREX-D Capsules with alcohol and other CNS depressants may lead to additional reductions in alertness and impairment of CNS performance and should be avoided.

Drug Interactions

MAO inhibitors and beta-adrenergic agonists increase the effects of sympathomimetic amines. Concomitant use of sympathomimetic amines with MAO inhibitors can result in a hypertensive crisis (see CONTRAINDICATIONS). Because MAO inhibitors are long-acting, SEMPREX-D Capsules should not be taken with an MAO inhibitor or for 14 days after stopping use of an MAO inhibitor.

Because of their pseudoephedrine content, SEMPREX-D Capsules may reduce the antihypertensive effects of drugs that interfere with sympathetic activity. Care should be taken in the administration of SEMPREX-D Capsules concomitantly with other sympathomimetic amines because the combined effects on the cardiovascular system may be harmful to the patient

Concomitant administration of SEMPREX-D Capsules with alcohol and other CNS depressants may result in additional reductions in alertness and impairment of CNS performance and should be avoided.

No formal drug interaction studies between SEMPREX-D Capsules and other possibly co-administered drugs have been performed.

Carcinogenesis, Mutagenesis, And Impairment Of Fertility

Carcinogenicity studies with the combination of acrivastine and pseudoephedrine have not been performed. Oral doses of acrivastine alone at levels up to 40 mg/kg/day (236 mg/m^2/day or 10 times the recommended human daily dose) for 20 to 22 months in rats and up to 250 mg/kg/day (750 mg/m^2/day or 32 times the recommended human daily dose) for 20 to 24 months in mice revealed no evidence of carcinogenic potential. No evidence of mutagenicity (with or without metabolic activation) was observed in the Ames Salmonella mutagenicity assay or in the L5178Y/tk+/- mouse lymphoma assay. In an in vitro cytogenetic study performed in cultured human lymphocytes, acrivastine induced structural chromosomal abnormalities in the absence of metabolic activation, but not in its presence. In an in vivo cytogenetic study in rats given single oral doses of acrivastine up to 1000 mg/kg (5900 mg/m^2 or 249 times the recommended human daily dose) there were no structural chromosomal alterations.

Reproduction-fertility studies in rats given acrivastine alone at levels up to 200 mg/kg/day (1180 mg/m^2/day or 50 times the recommended human daily dose) had no effect on male or female fertility. Similarly, no effect on fertility was seen in male rats given acrivastine 20 mg/kg/day and pseudoephedrine 100 mg/kg/ day (118 and 590 mg/m^2/day or 5 and 3 times the recommended human daily doses, respectively) or in female rats given acrivastine 4 mg/kg/day and pseudoephedrine 20 mg/kg/day (23.6 and 118 mg/m^2/day or 1 and 0.7 times the recommended human daily doses, respectively).

Pregnancy

Pregnancy Category B

Teratogenic Effects

No evidence of teratogenicity was seen in rats and rabbits given acrivastine 1000 and 400 mg/kg/day, respectively (5900 and 4720 mg/m^2/day or 249 and 200 times the recommended human daily dose). No evidence of teratogenicity was seen in rats given a combination of acrivastine 30 mg/kg/day and pseudoephedrine 150 mg/kg/day (177 and 885 mg/m^2/day or 8 and 5 times the recommended human daily dose, respectively). Similarly, no evidence of teratogenicity was observed in rabbits given acrivastine 20 mg/kg/day and pseudoephedrine 100 mg/kg/day (236 and 1180 mg/m^2/day or 10 and 7 times the recommended human daily doses, respectively). There are, however, no adequate and well-controlled studies in pregnant women. Because animal teratology studies are not always predictive of human responses, SEMPREX-D Capsules should be used during pregnancy only if the potential benefit justifies the potential risks to the fetus.

Nonteratogenic Effects

In a perinatal-postnatal study in rats, acrivastine given alone at levels up to 500 mg/kg/day (2950 mg/m^2/day or 124 times the recommended human daily dose) was associated with maternal and neonatal mortality at the maximum dose level. Neonatal survival was decreased in rats given a combination of acrivastine 20 mg/kg/day and pseudoephedrine 100 mg/ kg/day (118 and 590 mg/m^2/day or 5 and 3 times the human dose, respectively).

Nursing Mothers

It is not known whether acrivastine is excreted in human milk; pseudoephedrine is excreted in human milk. SEMPREX-D Capsules should only be used in nursing mothers when the potential benefit justifies the potential risks to the nursing infant.

Pediatric Use

Safety and effectiveness of SEMPREX-D Capsules in pediatric patients under the age of 12 years have not been established.

Geriatric Use

Of the total number of subjects in clinical studies of SEMPREX-D, 349 were 60 years of age or older and 53 were 70 years of age and older. No overall differences in safety or effectiveness were observed between these subjects and younger subjects, and other reported clinical experience has not identified differences in responses between the elderly and younger patients, but greater sensitivity of some older individuals cannot be ruled out. Antihistamines, however, as a pharmaceutical class, are more likely to cause dizziness, sedation, bladder-neck obstruction, and hypotension in elderly patients. The elderly are also more likely to have adverse reactions to sympathomimetics such as pseudoephedrine (see CLINICAL PHARMACOLOGY and WARNINGS).

This drug is known to be substantially excreted by the kidney, and the risk of toxic reactions to this drug may be greater in patients with impaired renal function. Because elderly patients are more likely to have decreased renal function, care should be taken in dose selection, and it may be useful to monitor renal function. Use of SEMPREX-D in patients with renal impairment (creatinine clearance ≤ 48 mL/min) is not recommended (see PRECAUTIONS, Use In Patients With Diminished Renal Function).

ADVERSE EXPERIENCES

Information on the incidence of adverse events in clinical investigations conducted in the U.S. was obtained from 33 controlled and 15 uncontrolled clinical studies in which 2499 patients received acrivastine and 2631 patients received acrivastine plus pseudoephedrine hydrochloride for treatment periods ranging from one day to one year. The majority of patients in clinical trials were exposed to acrivastine or acrivastine plus pseudoephedrine for less than 90 days. Acrivastine dosage ranged from 3 to 96 mg/day; 1336 patients received dosages equal to or greater than acrivastine 24 mg/day. Acrivastine plus pseudoephedrine hydrochloride dosages ranged from acrivastine 8 to 48 mg/day plus pseudoephedrine hydrochloride 60 to 240 mg/day. A total of 2335 patients received three or four daily doses of acrivastine 8 mg plus pseudoephedrine hydrochloride 60 mg.

In controlled clinical trials, only 12 spontaneously elicited adverse events were reported with frequencies greater than 1% in the acrivastine plus pseudoephedrine hydrochloride treatment group (see table).

TABLE 1 ADVERSE EVENTS REPORTED IN CLINICAL TRIALS* (PERCENT OF PATIENTS REPORTING)†
 | Controlled Studies
 | Placebo (N = 1767) | Acrivastine (N = 1935) | Pseudoephedrine (N = 887) | Acrivastine plus Pseudoephedrine (N = 1650)
CNS
Somnolence‡ | 6 | 12 | 8 | 12
Headache | 18 | 19 | 19 | 19
Dizziness | 2 | 3 | 3 | 3
Nervousness‡ | 1 | 2 | 4 | 3
Insomnia‡ | 1 | 1 | 6 | 4
MISCELLANEOUS
Nausea | 2 | 3 | 3 | 2
Dry Mouth‡ | 2 | 3 | 5 | 7
Asthenia | 2 | 3 | 2 | 2
Dyspepsia | 1 | 1 | 2 | 2
Pharyngitis | 2 | 1 | 1 | 3
Cough Increase | 1 | 2 | 1 | 2
Dysmenorrhea | 1 | 2 | 3 | 2
*Includes all events regardless of casual relationship to treatment.
†Includes all adverse events with a reported frequency of > 1% for the acrivastine plus pseudoephedrine treatment group.
‡SEMPREX-D demonstrates a statistically higher frequency of events than placebo, p ≤ 0.05.

The nature and overall frequencies of adverse events from international clinical trials (35 studies involving approximately 1600 patients) were similar to the results obtained in the U.S. studies.

Post-marketing clinical experience reports with acrivastine and acrivastine plus pseudoephedrine have included rare serious hypersensitivity reactions manifested by anaphylaxis, angioedema, bronchospasm, and erythema multiforme. No deaths associated with use of acrivastine or acrivastine plus pseudoephedrine have been reported.

Pseudoephedrine may cause ephedrine-like reactions such as tachycardia, palpitations, headache, dizziness, or nausea (see WARNINGS and OVERDOSAGE).

OVERDOSAGE

There have been no reports of overdosage with Semprex-D Capsules. In the clinical trial program and in international post-marketing experience, there have been two reported overdoses with acrivastine. Doses were 72 mg and 322 mg. Both patients recovered without sequelae. Adverse events included trembling, stridor, loss of consciousness and possible convulsions in the first patient and somnolence in the second.

Since acrivastine and pseudoephedrine have pharmacologically different actions, it is difficult to predict how an individual will respond to overdosage with SEMPREX-D Capsules. However, acute overdosage with SEMPREX-D Capsules may produce clinical signs of either CNS stimulation or depression. Overdosage of sympathomimetics has been associated with the following events: fear, anxiety, tenseness, restlessness, tremor, weakness, pallor, respiratory difficulty, dysuria, insomnia, hallucinations, convulsions, CNS depression, arrhythmias, and cardiovascular collapse with hypotension. Treatment for overdosage with SEMPREX-D Capsules should follow general symptomatic and supportive principles.

In a placebo-controlled, double-blind clinical trial in 18 healthy male subjects, single doses of acrivastine up to 400 mg (50 times the recommended antihistaminic dose) produced only a weak vagolytic effect, manifested as an increase in heart rate, and did not cause cardiac repolarization delays (i.e., increased QTc). Daily doses of acrivastine up to 2400 mg (75 times the recommended antihistamine dose) in an uncontrolled study in 38 cancer patients produced a 15-beats-per-minute increase in mean heart rate and occasional episodes of nausea and vomiting. The effects of acrivastine plus pseudoephedrine at single or multiple doses higher than the recommended daily dose of SEMPREX-D Capsules (i.e., 32 mg acrivastine plus 240 mg pseudoephedrine) on heart rate and cardiac repolarization have not been investigated in clinical trials.

The mean LD50 (single, oral dose) of acrivastine is greater than 4000 mg/kg (23600 mg/m^2 or 1000 times the recommended human daily dose) in rats and greater than 1200 mg/kg (3600 mg/m^2 or 153 times the recommended human daily dose) in mice. The mean LD50 (single, oral dose) of pseudoephedrine hydrochloride is 2206 mg/kg (13015 mg/m^2 or 73 times the recommended human daily dose) in rats and 726 mg/kg (2178 mg/m^2 or 12 times the recommended human daily dose) in mice. The toxic and lethal concentrations of acrivastine and pseudoephedrine in human biologic fluids are not known. Based upon pharmacokinetic screening data from clinical trials, the maximum plasma acrivastine concentration after dosing with acrivastine 8 mg was 393 ng/mL and the maximum plasma pseudoephedrine concentration after dosing with pseudoephedrine hydrochloride 60 mg was 1308 ng/mL.

DOSAGE AND ADMINISTRATION

The recommended dosage for adults and adolescents 12 years and older is one capsule administered orally, every 4 to 6 hours four times a day.

HOW SUPPLIED

SEMPREX-D Capsules (dark green opaque cap and white opaque body with a yellow band) contain acrivastine 8 mg and pseudoephedrine hydrochloride 60 mg. The cap is printed with “404” in white ink, and the body is printed with “SEMPREX-D” in black ink.

NDC 53014-404-10 Bottle of 100’s

Storage

Store at 15° to 25° C (59° to 77° F) in a dry place and protected from light.

Keep out of the reach of children.

For Medical Information

Contact: Medical Affairs Department
Phone: (866) 822-0068
Fax: (770) 970-8859

Marketed by:

UCB, Inc.
Smyrna, GA 30080

Manufactured by:
DSM Pharmaceuticals, Inc.
Greenville, NC 27834 USA

SEMPREX is a registered trademark of UCB, Inc., Smyrna, GA 30080
© 2007, UCB, Inc., Smyrna, GA 30080
All rights reserved.

Rev. 1E 07/2007
003419